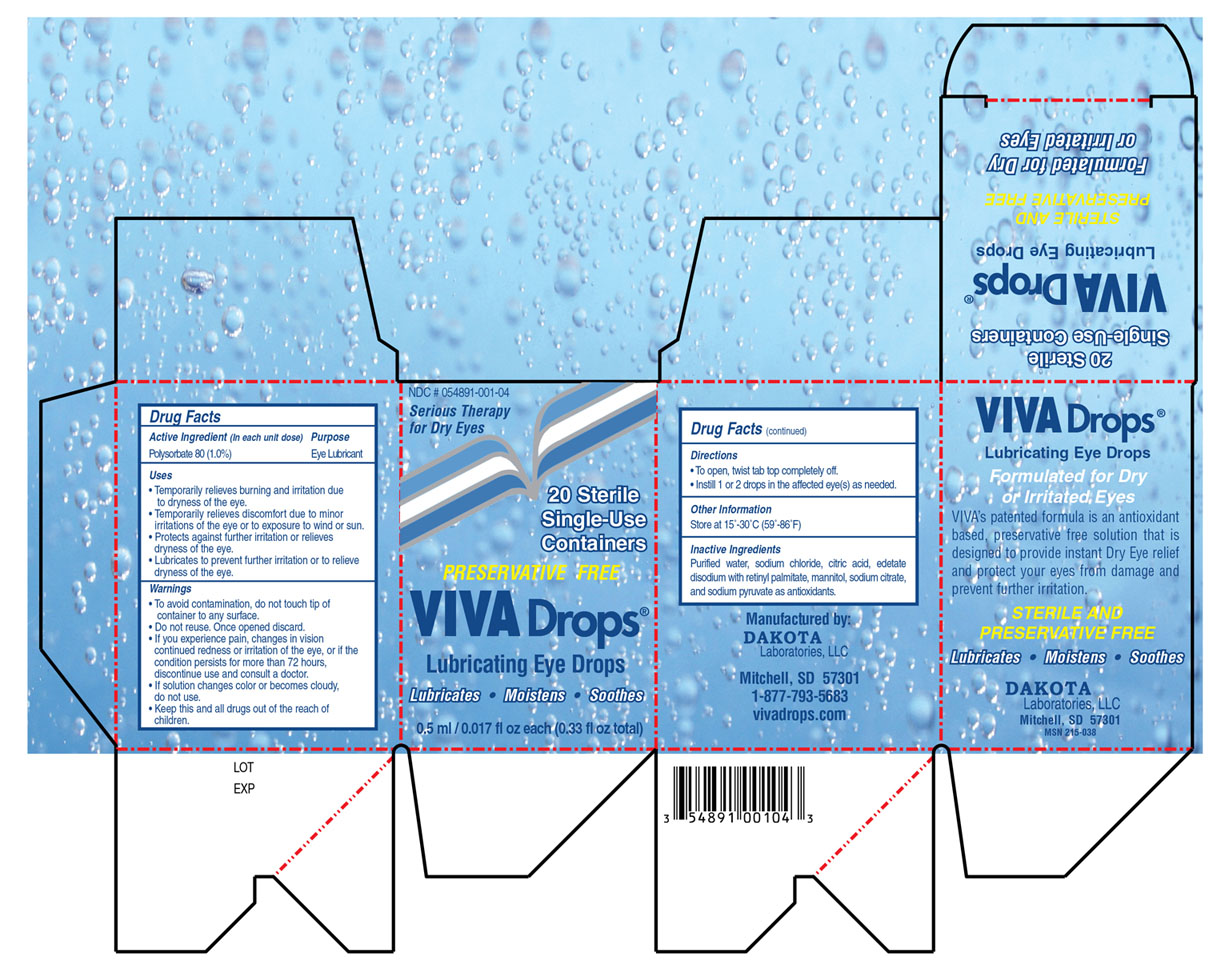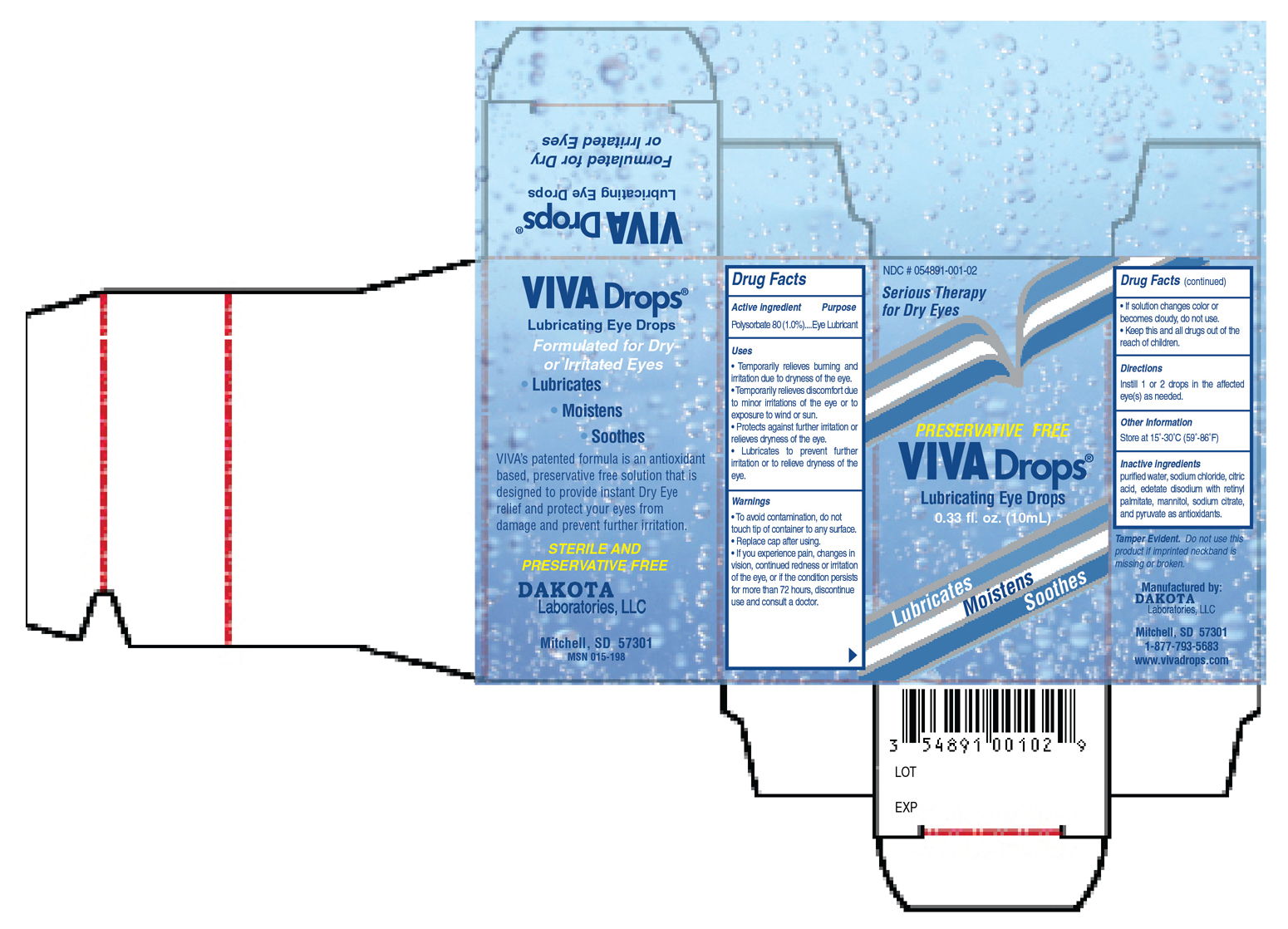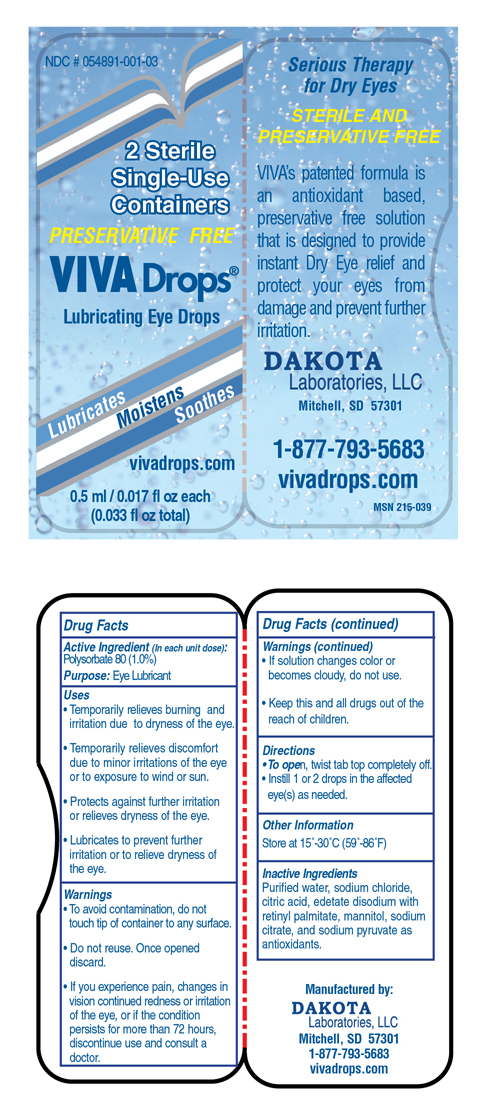 DRUG LABEL: Viva
NDC: 54891-001 | Form: SOLUTION/ DROPS
Manufacturer: Dakota Laboratories, LLC
Category: otc | Type: HUMAN OTC DRUG LABEL
Date: 20120125

ACTIVE INGREDIENTS: Polysorbate 80 100 mg/10 mL
INACTIVE INGREDIENTS: WATER; SODIUM CHLORIDE 60.5 mg/10 mL; Citric Acid .34 mg/10 mL; Edetate Disodium 5 mg/10 mL; VITAMIN A PALMITATE 5.5 mg/10 mL; Mannitol 18 mg/10 mL; Sodium Citrate 73.6 mg/10 mL; Sodium Pyruvate 5 mg/10 mL

Drug Facts

Active ingredients

Polysorbate 80 (1.0%)

Purpose

Eye Lubricant

Keep out of reach of children

• Keep this and all drugs out of the reach of children.

INDICATIONS AND USAGE

• Temporarily relieves burning and irritation due to dryness of the eye.
• Temporarily relieves discomfort due to minor irritations of the eye or to exposure to wind or sun.
• Protects against further irritation or relieves dryness of the eye.
• Lubricates to prevent further irritation or to relieve dryness of the eye.

WARNINGS

• To avoid contamination, do not touch tip of container to any surface.

• Replace cap after using

• If you experience pain, changes in vision, continued redness or irritation of the eye, or if the condition persists for more than 72 hours, discontinue use and consult a doctor.

• If solution changes color or becomes cloudy, do not use.

DOSAGE AND ADMINISTRATION

Instill 1 or 2 drops in the affected eye(s) as needed.

INACTIVE INGREDIENT

purified water, sodium chloride, citric acid, edetate disodium with retinyl palmitate, mannitol, sodium citrate, and pyruvate as antioxidants.